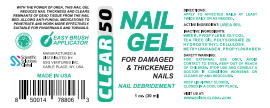 DRUG LABEL: Clear 50 Nail Gel
NDC: 81376-611 | Form: GEL
Manufacturer: SSG Ventures Inc
Category: otc | Type: HUMAN OTC DRUG LABEL
Date: 20210427

ACTIVE INGREDIENTS: UREA 50 g/100 mL
INACTIVE INGREDIENTS: PROPYLENE GLYCOL; METHYLPARABEN; WATER; TEA TREE OIL; POLYSORBATE 20; HYDROXYETHYL CELLULOSE, UNSPECIFIED; PROPYLPARABEN

Clear 50 Nail Gel

PACKAGE LABEL

ACTIVE INGREDIENT

Urea 50%

PURPOSE

WITH THE POWER OF UREA, THIS NAIL GEL REDUCES NAIL THICKNESS AND CLEARS REMNANTS OF DEAD TISSUE FROM THE NAIL BED. ALLOWS ANTI-FUNGAL MEDICATIONS TO PENETRATE AND WORK MORE EFFECTIVELY. SUITABLE FOR FINGERNAILS AND TOENAILS

INDICATIONS AND USAGE

FOR DAMAGED AND THICKENED NAILS

SAFE HANDLING WARNING

FOR EXTERNAL USE ONLY.

AVOID CONTACT TO EYES.

KEEP OUT OF REACH OF CHILDREN.

STOP USE AND CONSULT A DOCTOR IF CONDITION WORSENS OR CLEARS UP AND REOCCURS

KEEP LID FIRMLY CLOSED.

CLOSED IN A COOL DRY PLACE

KEEP OUT OF REACH OF CHILDREN

DOSAGE AND ADMINISTRATION

APPLY TO AFFECTED NAILS AT LEAST TWICE DAILY OR AS NEEDED

INACTIVE INGREDIENT

WATER, PROPYLENE GLYCOL, TEA TREE OIL POLYSORBATE 20, HYDROXYETHYL CELLULOSE, METHYLPARABEN, PROPYLPARABEN

STORAGE AND HANDLING

KEEP LID FIRMLY CLOSED

CLOSED IN A COOL DRY PLACE

WARNINGS

FOR EXTERNAL USE ONLY.

AVOID CONTACT TO EYES.

KEEP OUT OF REACH OF CHILDREN

STOP USE AND CONSULT DOCTOR IF CONDITION WORSENS OR CLEARS US AND REOCCURS